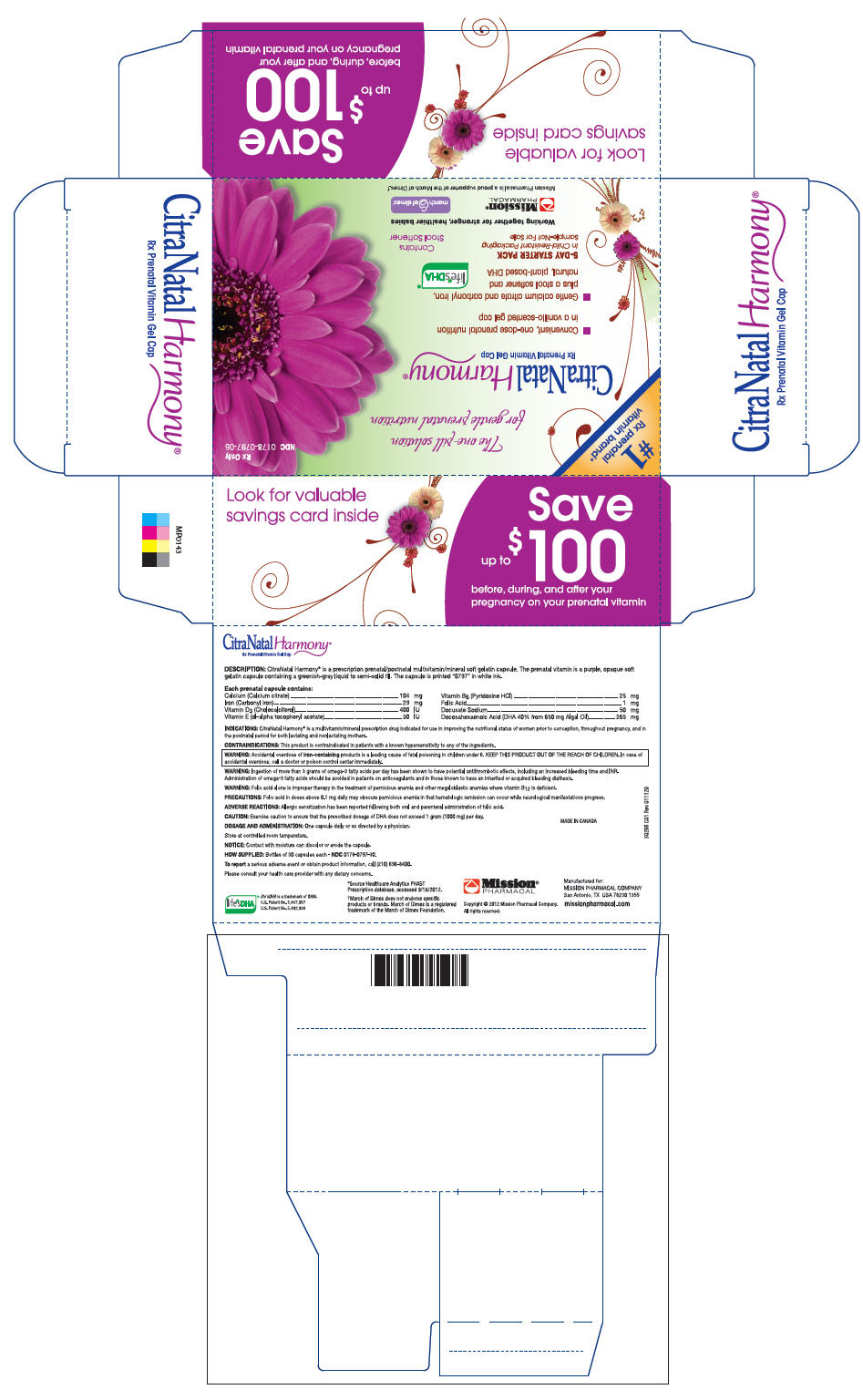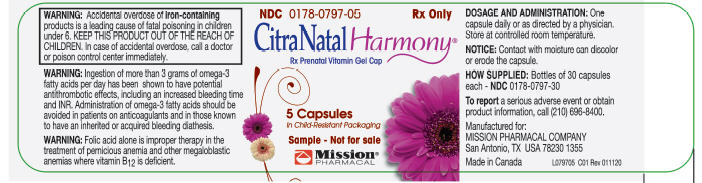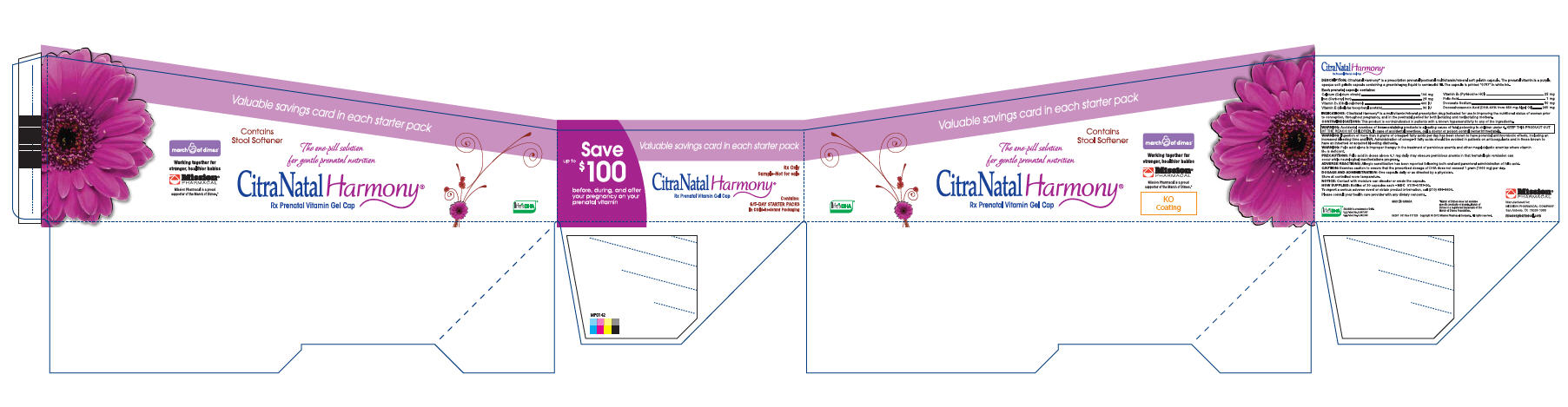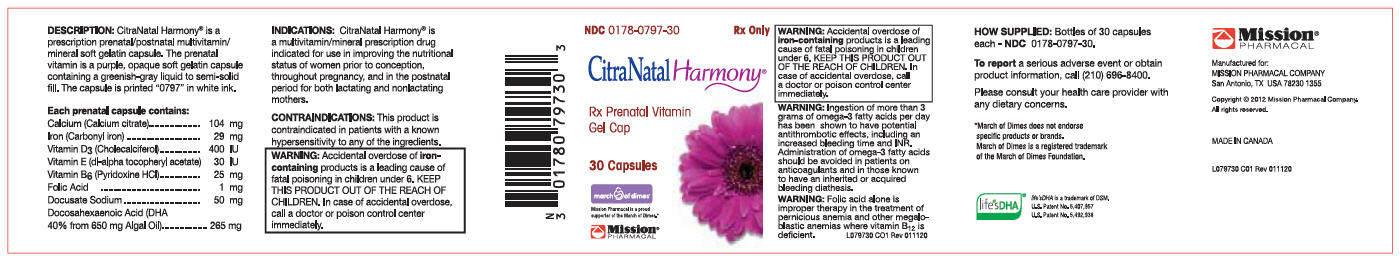 DRUG LABEL: Citranatal Harmony 2.1
NDC: 0178-0797 | Form: CAPSULE, GELATIN COATED
Manufacturer: Mission Pharmacal Company
Category: prescription | Type: HUMAN PRESCRIPTION DRUG LABEL
Date: 20190514

ACTIVE INGREDIENTS: CALCIUM CITRATE 104 mg/1 1; IRON 29 mg/1 1
INACTIVE INGREDIENTS: CHOLECALCIFEROL 400 [iU]/1 1; .ALPHA.-TOCOPHEROL 30 [iU]/1 1; PYRIDOXINE 25 mg/1 1; FOLIC ACID 1 mg/1 1; DOCUSATE SODIUM 50 mg/1 1; DOCONEXENT 265 mg/1 1

These highlights do not include all the information needed to use CitraNatal Harmony® safely and effectively. See full prescribing information for CitraNatal Harmony®.
CitraNatal Harmony® (Calcium citrate, Iron pentacarbonyl, Cholecalciferol, .Alpha.-Tocopherol, Dl-, Pyridoxine hydrochloride, Folic Acid, Docusate Sodium, and Doconexent) capsules for oral use.
Initial U.S. Approval: 2012

WARNING

Accidental overdose of iron-containing products is a leading cause of fatal poisoning in children under 6. KEEP THIS PRODUCT OUT OF THE REACH OF CHILDREN. In case of accidental overdose, call a doctor or poison control center immediately.

DESCRIPTION

CitraNatal Harmony® is a prescription prenatal/postnatal multivitamin/mineral soft gelatin capsule. The prenatal vitamin is a purple, opaque soft gelatin capsule containing a greenish-gray liquid to semi-solid fill. The capsule is printed “0797” in white ink.

Each prenatal capsule contains:
Calcium (Calcium citrate) | 104 mg | Vitamin B6 (Pyridoxine HCI) | 25    mg
Iron (Carbonyl iron) | 29 mg | Folic Acid | 1    mg
Vitamin D3 (Cholecalciferol) | 400 |U | Docusate Sodium | 50    mg
Vitamin E (d|-alpha tocopheryl acetate) | 30 |U | Docosahexaenoic Acid (DHA 40% from 650 mg Algal Oil) | 265    mg

INDICATIONS

CitraNatal Harmony® is a multivitamin/mineral prescription drug indicated for use in improving the nutritional status of women prior to conception, throughout pregnancy, and in the postnatal period for both lactating and nonlactating mothers.

CONTRAINDICATIONS

This product is contraindictated in patients with a known hypersensitivity to any of the ingredients.

WARNING

Ingestion of more than 3 grams of omega-3 fatty acids per day has been shown to have potential antithrombotic effects, including an increased bleeding time and INR. Administration of omega-3 fatty acids should be avoided in patients on anticoagulants and in those known to have an inherited or acquired bleeding diathesis.

WARNING

Folic acid alone is improper therapy in the treatment of pernicious anemia and other megaloblastic anemias where vitamin B12 is deficient.

PRECAUTIONS

Folic acid in doses above 0.1 mg daily may obscure pernicious anemia in that hematologic remission can occur while neurological manifestations progress.

ADVERSE REACTIONS

Allergic sensitization has been reported following both oral and parenteral administration of folic acid.

CAUTION

Exercise caution to ensure that the prescribed dosage of DHA does not exceed 1 gram (1000 mg) per day.

DOSAGE AND ADMINISTRATION

One capsule daily or as directed by a physician.

Store at controlled room temperature.

NOTICE

Contact with moisture can discolor or erode the capsule.

HOW SUPPLIED

Bottles of 30 capsules each — NDC 0178–0797–30

To report a serious adverse event or obtain product information, call (210) 696–8400

Please consult your health care provider with any dietary concerns.

Manufactured for:
MISSION PHARMACAL COMPANY
San Antonio, TX USA 78230 1355

PACKAGE LABEL

CitraNatal Sample Carton
NDC 0178-0797-06

CitraNatal Label
NDC 0178-0797-05

PACKAGE LABEL

CitraNatal Starter Pack

CitraNatal Label
NDC 0178-0797-30